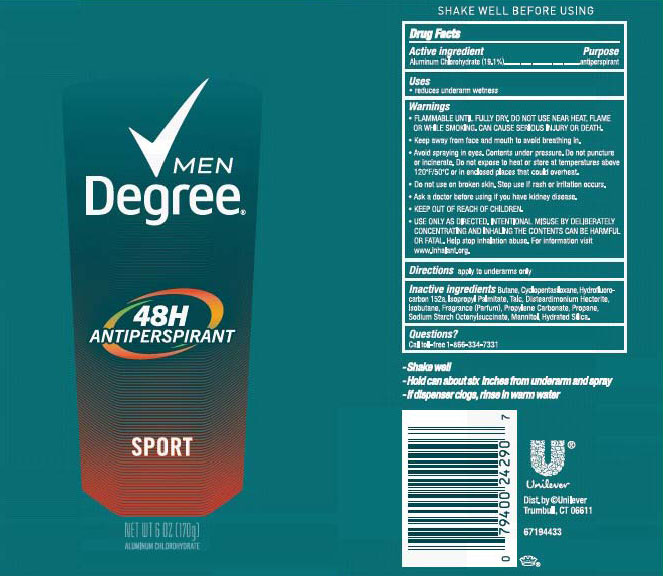 DRUG LABEL: Degree
NDC: 64942-1558 | Form: AEROSOL, SPRAY
Manufacturer: Conopco Inc. d/b/a Unilever
Category: otc | Type: HUMAN OTC DRUG LABEL
Date: 20171024

ACTIVE INGREDIENTS: ALUMINUM CHLOROHYDRATE 19.1 g/100 g
INACTIVE INGREDIENTS: BUTANE; 1,1-DIFLUOROETHANE; CYCLOMETHICONE 5; ISOBUTANE; ISOPROPYL PALMITATE; TALC; DISTEARDIMONIUM HECTORITE; PROPANE; PROPYLENE CARBONATE; HYDRATED SILICA; MANNITOL

Degree Men Sport 48H Antiperspirant

DEGREE MEN SPORT 48H ANTIPERSPIRANT - aluminum chlorohydrate aerosol, spray

Degree Men Sport 48H Antiperspirant

Drug Facts

Active Ingredient:

Aluminum Chlorohydrate (19.1%)

Purpose:

antiperspirant

Uses

reduces underarm wetness

Warnings

• FLAMMABLE UNTILFULLY DRY. DO NOT USE NEAR HEAT, FLAME, OR WHILE SMOKING. CAN CAUSE SERIOUS INJURY OR DEATH.
• Keep away from face and mouth to avoid breathing in.
• Avoid spraying in eyes. Contents under pressure. Do not puncture or incinerate. Do not expose to heat or store at temperatures above 120°F/50°C or in enclosed places that could overheat.
• Do not use on broken skin. Stop use if rash or irritation occurs.
• Ask a doctor before using if you have kidney disease.
• USE ONLY AS DIRECTED. INTENTIONAL MISUSE BY DELIBERATELY CONCENTRATING AND INHALING THE CONTENTS CAN BE HARMFUL OR FATAL.
Help stop inhalation abuse. For information visit www.inhalant.org

• KEEP OUT OF REACH OF CHILDREN

Directions

Apply to underarms only

Inactive ingredients

Butane, Cyclopentasiloxane, Hydrofluorocarbon 152a, Isopropyl Palmitate, Talc, Disteardimonium Hectorite, Isobutane, Fragrance (Parfum), Propylene Carbonate, Propane, Sodium Starch Octenylsuccinate, Mannitol, Hydrated Silica

Questions?

Call toll-free 1-866-334-7331

INSTRUCTIONS FOR USE

- Shake well

- Hold can about six inches from underarm and spray

- If dispenser clogs, rinse in warm water